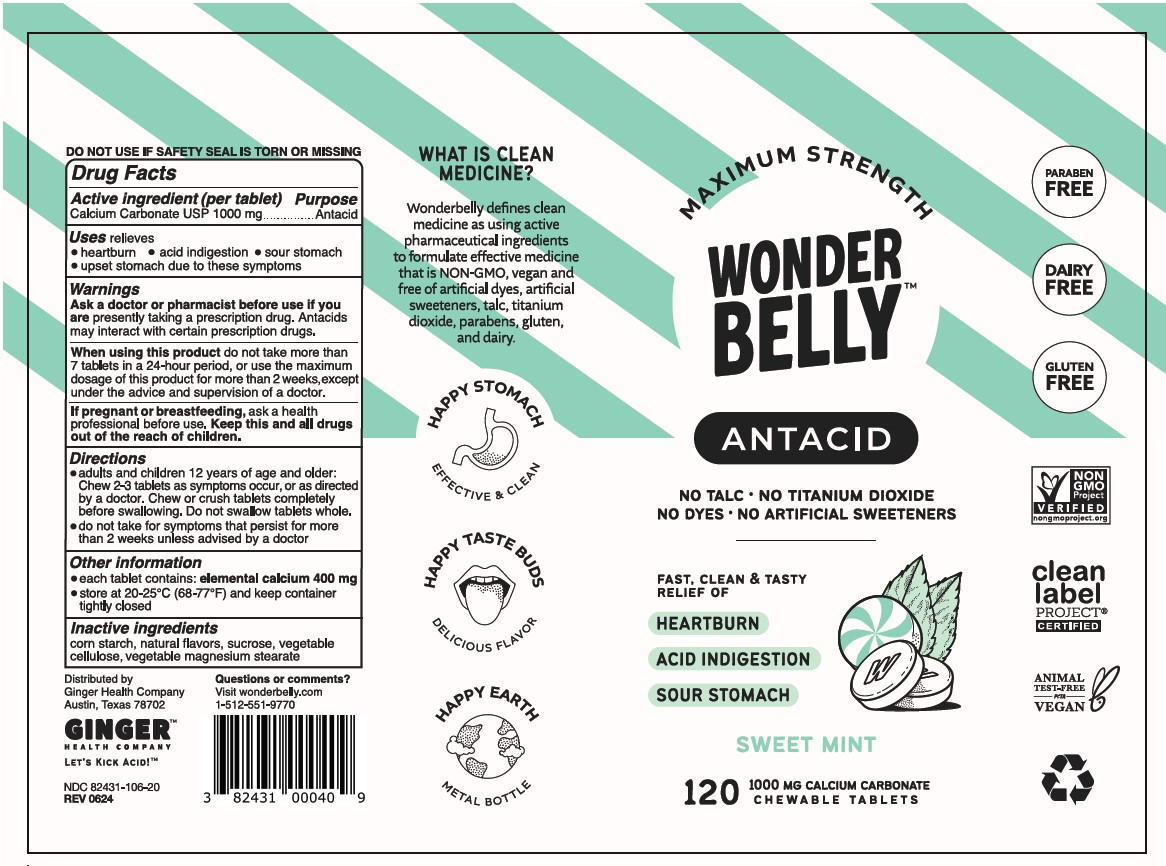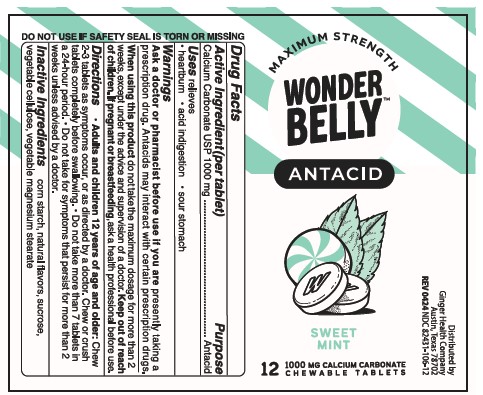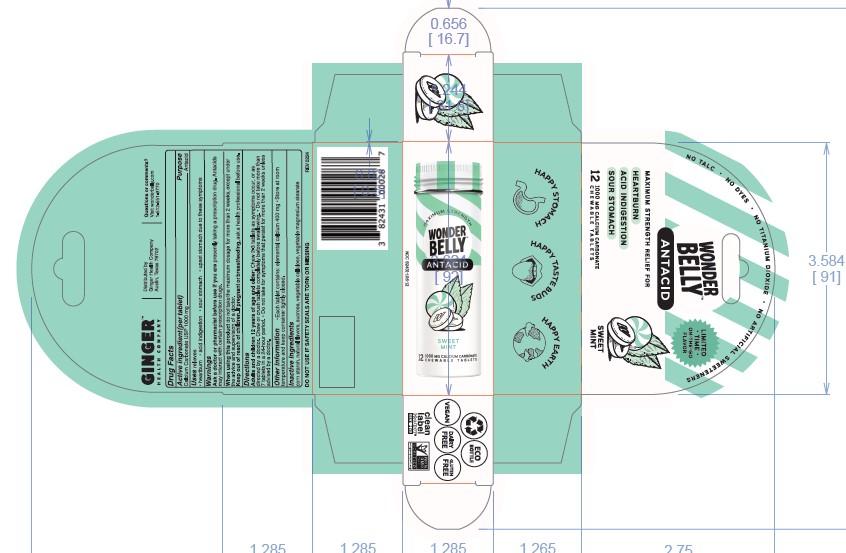 DRUG LABEL: Wonderbelly Maximum Strength Antacid - Sweet Mint
NDC: 82431-106 | Form: TABLET, CHEWABLE
Manufacturer: Ginger Health Company
Category: otc | Type: HUMAN OTC DRUG LABEL
Date: 20240729

ACTIVE INGREDIENTS: CALCIUM CARBONATE 1000 mg/1 1
INACTIVE INGREDIENTS: MAGNESIUM STEARATE; MICROCRYSTALLINE CELLULOSE; SUCROSE; STARCH, CORN

Sweet Mint Antacid

Active ingredient (per tablet)

Calcium Carbonate USP 1000mg

Purpose

Antacid

Uses

relieves

heartburn

acid indigestion

sour stomach

upset stomach associated with these symptoms

Warnings

Ask a doctor or pharmacists before use if you are presently taking a prescription drug. Antacids may interact with certain prescription drugs.

When using this product

do not take more than 7 tablets in 24 hours

do not use the maximum dosage for more than 2 weeks, except under the advice and supervision of a doctor

If pregnant or breast-feeding, ask a health professional before use

Keep out of reach of children.

Directions

adults and children 12 years of age and older; chew 2-3 tablets as symptoms occur, or as directed by a doctor. Chew or crush tablets completely before swallowing.

for best results, wet in mouth before chewing

do not take for symptoms that persist for more than 2 weeks unless advised by a doctor

Other Information

each tablet contains: elemental calcium 400mg

store at room temperature and keep container tightly closed

Inactive Ingredients

maize starch, natural flavors, sucrose, vegetable cellulose, vegetable magnesium stearate

12ct UC - REV 0224 12ct Bottle - REV 0224 120ct Bottle - REV 0624

Principal Display Panel-12ct UC Rev 0224

Principal Display panel-12ct Bottle Rev 0224

Principal Display Panel-120ct Sweet Mint Antacid Bottle Rev 0624